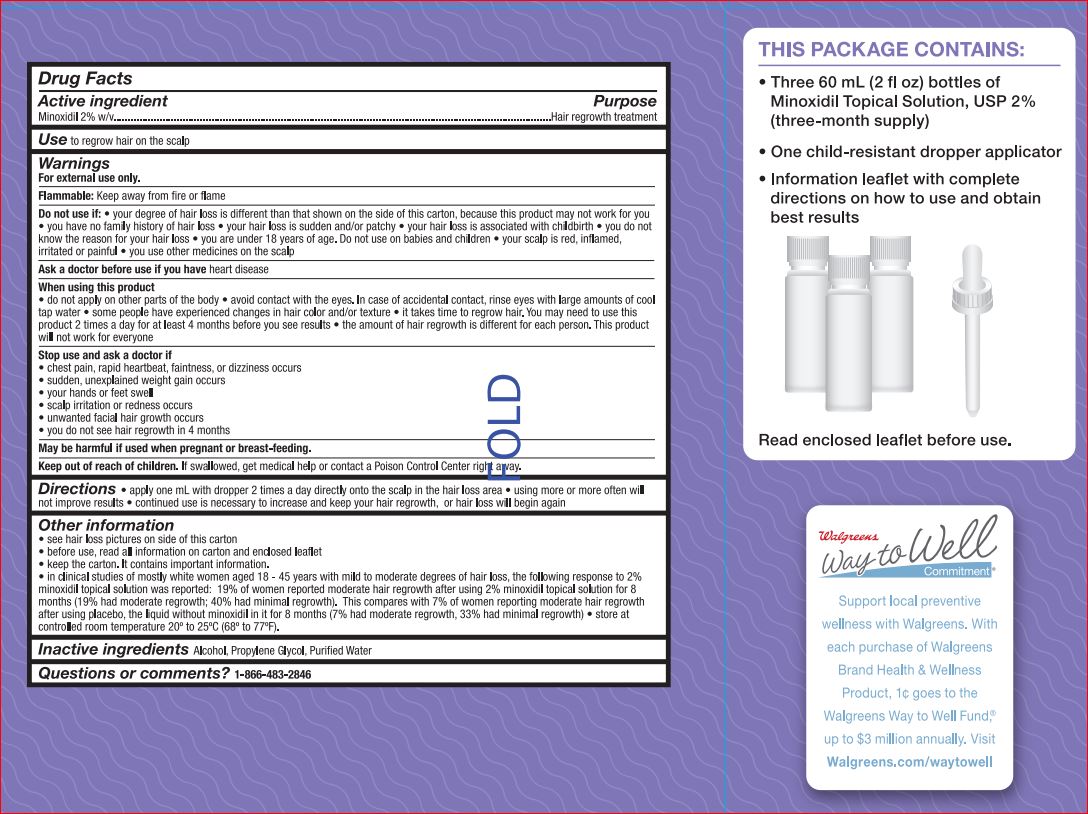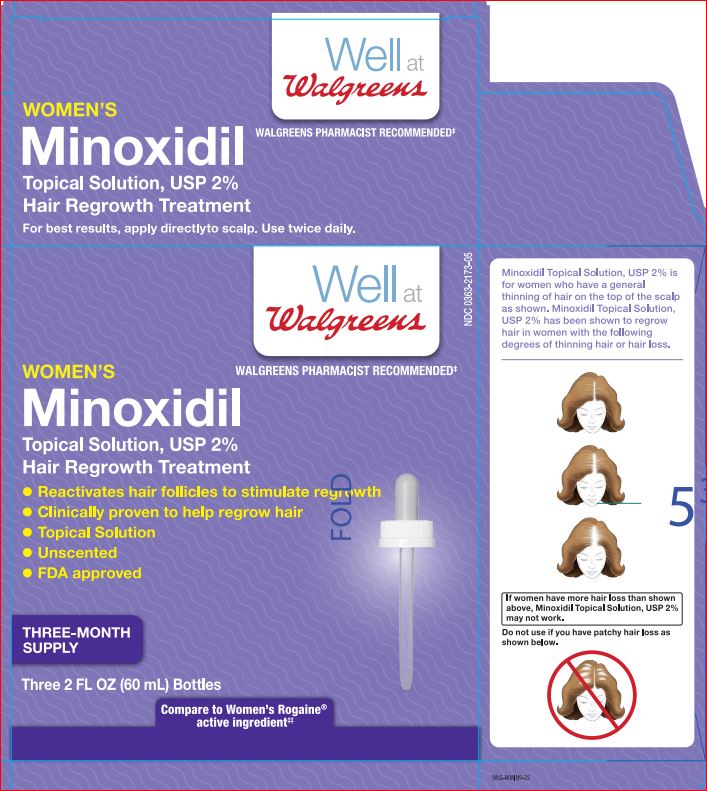 DRUG LABEL: Solution
NDC: 0363-2173 | Form: SOLUTION
Manufacturer: Walgreens
Category: otc | Type: HUMAN OTC DRUG LABEL
Date: 20171128

ACTIVE INGREDIENTS: MINOXIDIL 0.02 g/1 mL
INACTIVE INGREDIENTS: ALCOHOL; PROPYLENE GLYCOL; WATER

For Women Minoxidil Topical Solution USP 2% Hair Regrowth Treatment

Active Ingredient

Minoxidil 2% w/v..........................................................................................................Hair regrowth treatment

Use

To regrow hair on the scalp (vertex only, see picture on side of carton)

Warnings For external use only.

Flammable: Keep away from fire or flame

Do not use if:

- Your degree of hair loss is different than that shown on the side of this carton, because this product may not work for you
- You have no family history of hair loss
- Your hair loss is sudden and/or patchy
- Your hair loss is associated with childbirth
- You do not know the reason for your hair loss
- You are under 18 years of age. Do not use on babies and children
- Your scalp is red, inflamed, irritated or painful
- You use other medicines on the scalp

Ask a doctor before use if you have:

- Heart Disease

When using this product:

- Do not apply on other parts of the body
- Avoid contact with the eyes. In case of accidental contact, rinse eyes with large amounts of cool tap water
- Some people have experienced changes in hair color and/or texture
- It takes time to regrow hair. You may need to use this product 2 times a day for at least 4 months before you see results
- The amount of hair regrowth is different for each person. This product will not work for everyone

Stop use and ask a doctor if:

- Chest pain, rapid heartbeat, faintness, or dizziness occurs
- Sudden, unexplained weight gain occurs
- Your hands or feet swell
- Scalp irritation or redness occurs
- Unwanted facial hair growth occurs
- You do not see hair regrowth in 4 months

Keep out of reach of children.

If swallowed, get medical help or contact a Poison Control Center right away.

Other Information:

- See hair loss pictures on side of this carton
- Before use, read all information on carton and enclosed leaflet
- Keep the carton. It contains important information
- In clinical studies of mostly white women aged 18-49 years wiht mild to moderate degrees of hair loss, the following response to 2% minoxidil topical solution was reported: 19% of women reported moderate hair regrowth after using 2% minoxidil topical solution for 8 months (19% had moderate regrowth; 40% had minimal regrowth). This compares with 7% of women reporting moderate hair regrowth after using placebo, the liquid without minoxidil in it for 8 months (7% had moderate regrowth, 33% had minimal regrowth)
- Store at controlled room temperature 20o to 25oC (68o to 77oF). Keep tightly closed.

Directions:

- Apply one mL with dropper 2 times a day directly onto the scalp in the hair loss area
- Using more or more often will not improve results
- Continued use is necessary to increase and keep you hair regrowth, or hair loss will begin again

Inactive Ingredients

Alcohol, Propylene Glycol, Purified Water